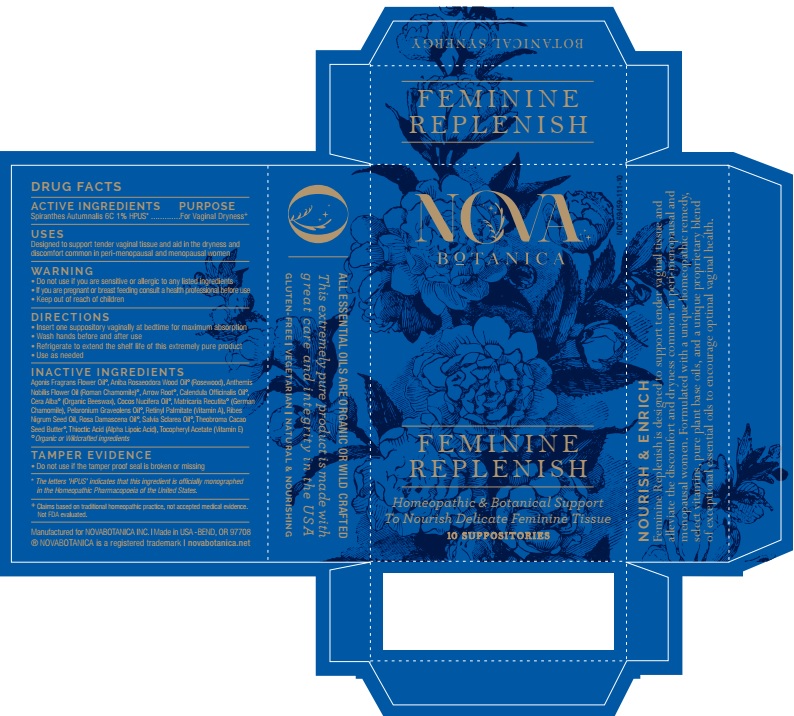 DRUG LABEL: Feminine Replenish
NDC: 69459-111 | Form: SUPPOSITORY
Manufacturer: Nova Botanica Inc.
Category: homeopathic | Type: HUMAN OTC DRUG LABEL
Date: 20181114

ACTIVE INGREDIENTS: SPIRANTHES SPIRALIS ROOT 6 [hp_C]/1 1
INACTIVE INGREDIENTS: FAGONIA ARABICA WHOLE; ROSEWOOD OIL; CHAMAEMELUM NOBILE FLOWER OIL; MARANTA ARUNDINACEA WHOLE; CALENDULA OFFICINALIS SEED OIL; WHITE WAX; COCONUT OIL; MATRICARIA RECUTITA; PELARGONIUM GRAVEOLENS FLOWER OIL; VITAMIN A; RIBES NIGRUM SEED OIL; ROSA DAMASCENA FLOWER OIL; SALVIA SCLAREA SEED OIL; COCOA BUTTER; THIOCTIC ACID; .ALPHA.-TOCOPHEROL

Feminine Replenish

ACTIVE INGREDIENTS

Spiranthes Autumnalis 6C 1% HPUS*

USES

Designed to support tender vaginal tissue and aid in the dryness and discomfort common in peri-menopausal and menopausal women.

WARNING

• Do not use if you are sensitive or allergic to any listed ingredients

• If you are pregnant or breast feeding consult a health professional before use

• Keep out of reach of children

• Keep out of reach of children.

DIRECTIONS

• Insert one suppository vaginally at bedtime for maximum absorption

• Wash hands before and afer use

• Refrigerate to extend the shelf life of this extremely pure product

• Use as needed

OTHER SAFETY INFORMATION

TAMPER EVIDENCE

• Do not use if the tamper proof seal is broken or missing.

INACTIVE INGREDIENT

Agonis Fragrans Flower Oil°, Aniba Rosaeodora Wood Oil° (Rosewood). Anthemis Nobilis Flower Oil° (Roman Chamomile)°, Arrow Root°, Calendula Officinalis Oil°, Cera Alba° (Organic Beeswax) Cocos Nucifera Oil°, Matricaria Recutita° (German Chamomile), Pelaronium Graveolens Oil°, Retinyl Palmimate (Vitamin A) Ribes Nigrum Seed Oil, Rosa Damascena Oil°, Salvia Sclarea Oil°, Theobroma Cocao Seed Butter°" Thioctic Acid (Alpha Lipoic Acid), Tocopheryl Acetate (Vitamin E) °Organic or Wilfcrafted Ingredients

QUESTIONS

Manufactured for NOVABOTANICA INC. ι Made in USA - Bend OR 97708

® NOVABOTANICA is a registered trademark ι novabotanica.net

PACKAGE LABEL

NOVA

BOTANICA

FEMININE

REPLENISH

Homeopathic & Botanical Support

To Nourish Delicate Feminine Tissue

10 SUPPOSITORIES

PURPOSE

For Vaginal Dryness+